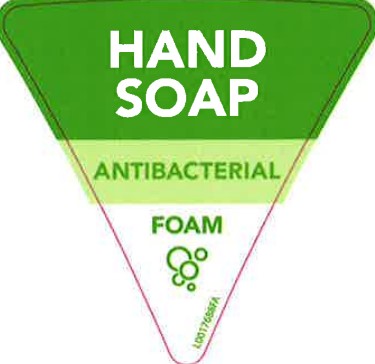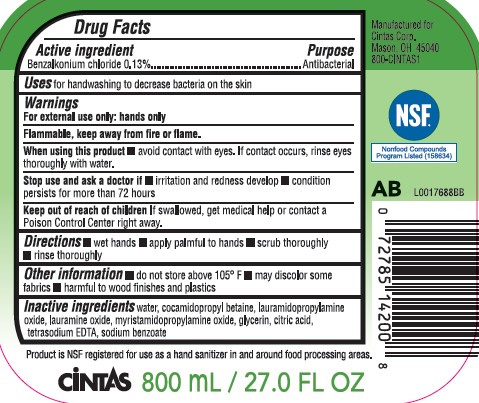 DRUG LABEL: Foaming Hand
NDC: 42961-224 | Form: LOTION
Manufacturer: Cintas Corporation
Category: otc | Type: HUMAN OTC DRUG LABEL
Date: 20260202

ACTIVE INGREDIENTS: BENZALKONIUM CHLORIDE 1.3 mg/1 mL
INACTIVE INGREDIENTS: WATER; COCAMIDOPROPYL BETAINE; LAURAMIDOPROPYLAMINE OXIDE; LAURAMINE OXIDE; MYRISTAMIDOPROPYLAMINE OXIDE; GLYCERIN; CITRIC ACID MONOHYDRATE; EDETATE SODIUM; SODIUM BENZOATE

Cintas 224.000/224AA
Antibacterial Foaming Hand Soap

Active ingredient

Benzalkonium chloride 0.13%

Purpose

Antibacterial

Uses

for handwashing to decrease bacteria on the skin

Warnings

for external use only: hands only

Flammable, keep away from fire or flame.

When using this product

- avoid contact with eyes. If contact occurs, rinse eyes thoroughly with water.

Stop use and ask a doctor if

- irritation and redness develop
- condition persists for more than 72 hours

Keep out of reach of children.

If swallowed, get medical help or contact a Poison Control Center immediately.

Directions

- wet hands
- apply palmful to hands
- scrub thoroughly
- rinse thoroughly

Other Information

- do not store above 105°F
- may discolor some fabrics
- harmful to wood finshes and plastics

Inactive ingredients

water, cocamidopropyl betaine, lauramidopropylamine oxide, lauramine oxide, myristamidopropylamine oxide, glycerin, citric acid, tetrasodium EDTA, sodium benzoate

ADVERSE REACTION

Product is NSF certified for use as a hand sanitizer in and around food processing areas.

CiNTAS

800mL/27.0 FL OZ

Manufactured for Cintas Corp.

Mason, OH 45040

800-CINTAS1

NSF Nonfood Compounds Program

principal display panel

HAND

SOAP

ANTIBACTERIAL

FOAM